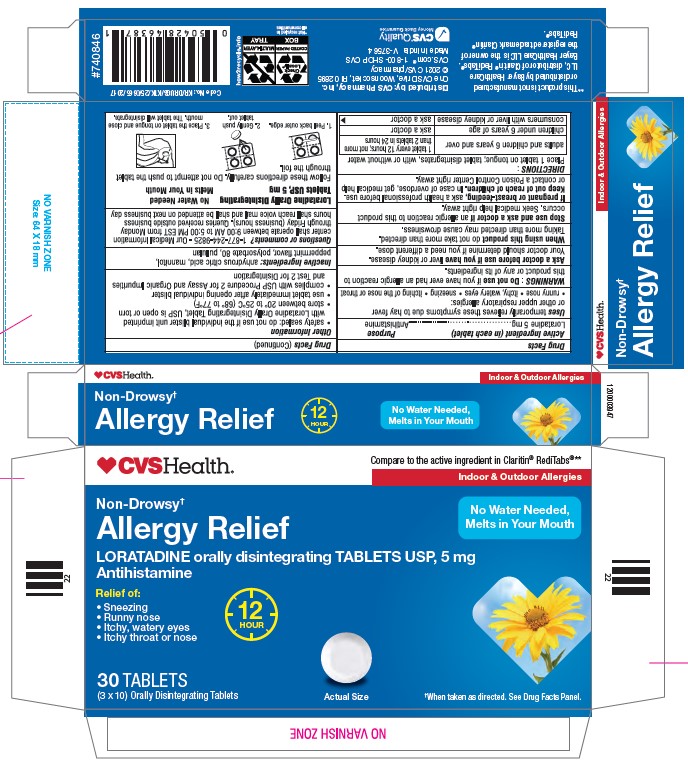 DRUG LABEL: LORATADINE
NDC: 51316-502 | Form: TABLET, ORALLY DISINTEGRATING
Manufacturer: CVS PHARMACY, INC
Category: otc | Type: HUMAN OTC DRUG LABEL
Date: 20241231

ACTIVE INGREDIENTS: LORATADINE 5 mg/1 1
INACTIVE INGREDIENTS: ANHYDROUS CITRIC ACID; PULLULAN; POLYSORBATE 80; MANNITOL

Loratadine Orally Disintegrating Tablets USP

Drug Facts

Active ingredient (in each tablet)

Loratadine 5 mg

Purpose

Antihistamine

Uses

temporarily relieves these symptoms due to hay fever or other upper respiratory allergies:

- runny nose
- itchy, watery eyes
- sneezing
- itching of the nose or throat

Warnings

Do not use if you have ever had an allergic reaction to this product or any of its ingredients.

Ask a doctor before use if you have liver or kidney disease. Your doctor should determine if you need a different dose.

When using this product do not take more than directed. Taking more than directed may cause drowsiness.

Stop use and ask a doctor if an allergic reaction to this product occurs. Seek medical help right away.

PREGNANCY OR BREAST FEEDING

If pregnant or breast-feeding, ask a health professional before use.

Keep out of reach of children. In case of overdose, get medical help or contact a Poison Control Center right away.

Directions

- place 1 tablet on tongue; tablet disintegrates, with or without water

adults and children 6 years and over | 1 tablet every 12 hours; not more than 2 tablets in 24 hours
children under 6 years of age | ask a doctor
consumers with liver or kidney disease | ask a doctor

Other information

- safety sealed: do not use if the individual blister unit imprinted with Loratadine Orally disintegrating Tablet, USP is open or torn
- store between 20° to 25°C (68° to 77°F)
- use tablet immediately after opening individual blister
- complies with USP Procedure 2 for Assay and Organic Impurities and Test 2 for Disintegration

Inactive ingredients

anhydrous citric acid, mannitol, peppermint flavor, polysorbate 80, pullulan

Questions or comments?

1-877-244-9825 - Our Medical Information center shall operate between 9:00 AM to 5:00 PM EST from Monday through Friday (business hours). Queries received outside business hours shall reach voice mail and shall be attended on next business day.

Manufactured by:

Tenshi Kaizen Private Limited

Bengaluru Rural – 562112, India

Distributed by:

CVS Pharmacy, Inc.

Revised: 09/2020